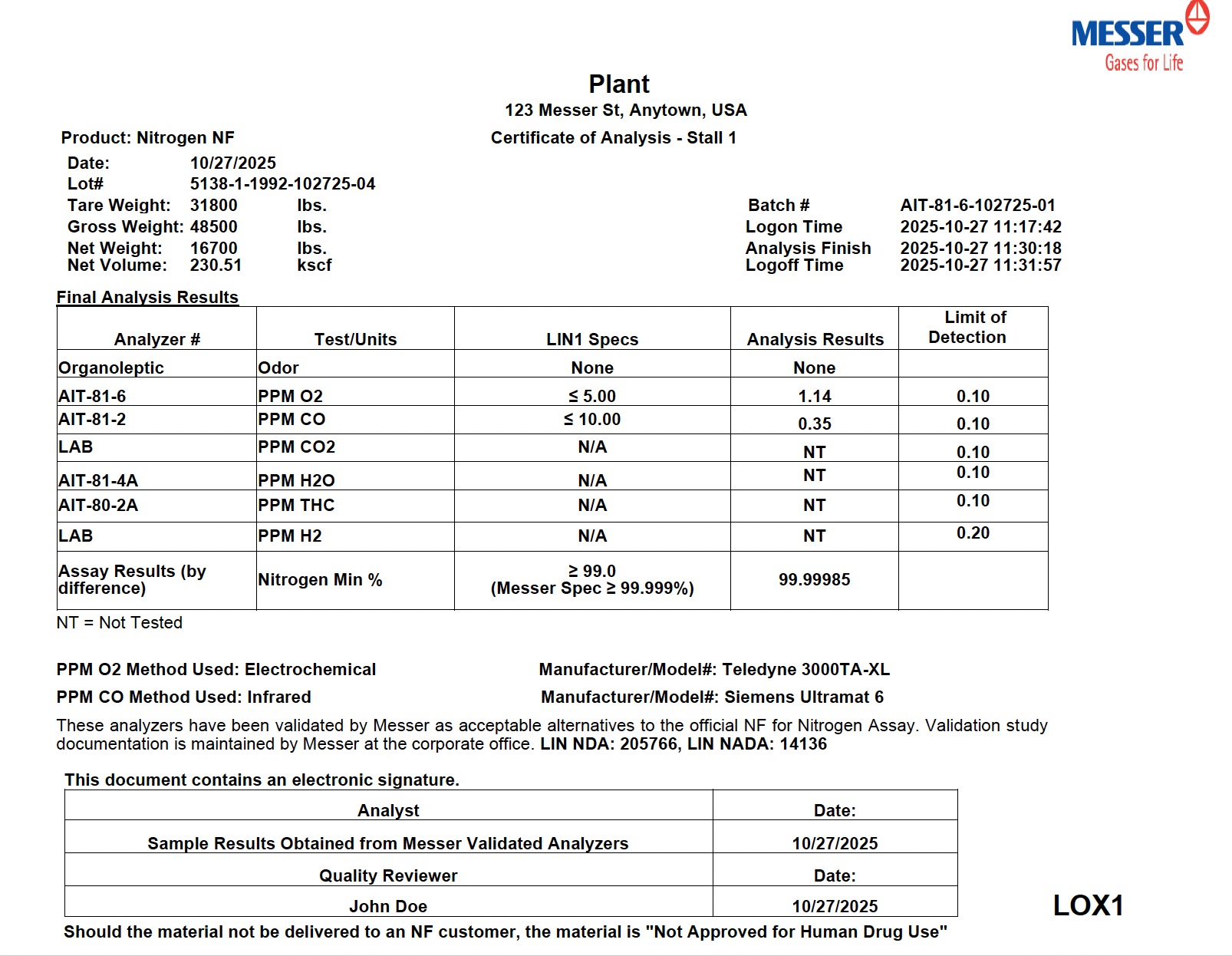 DRUG LABEL: Nitrogen
NDC: 52438-016 | Form: GAS
Manufacturer: Messer LLC
Category: prescription | Type: HUMAN PRESCRIPTION DRUG LABEL
Date: 20251112

ACTIVE INGREDIENTS: NITROGEN 995 mL/1 L

Messer LLC - Nitrogen NF Bulk Liquid

PACKAGE LABEL

Plant
123 Messer St, Anytown, USA

Certificate of Analysis - Stall 1

Product: Nitrogen NF
Date: 10/27/2025
Lot#: 5138-1-1992-102725-04
Tare Weight: 31800 lbs.
Gross Weight: 48500 lbs.
Net Weight: 16700 lbs.
Net Volume: 230.51 kscf

Batch #: AIT-81-6-102725-01
Logon Time: 2025-10-27 11:17:42
Analysis Finish: 2025-10-27 11:30:18
Logoff Time: 2025-10-27 11:31:57

Final Analysis Results

Analyzer #

Test/Units

LIN1 Specs

Analysis Results

Limit of Detection

Organoleptic

Odor

None

None

AIT-81-6

PPM O₂

≤ 5.00

1.14

0.10

AIT-81-2

PPM CO

≤ 10.00

0.35

0.10

LAB

PPM CO₂

N/A

NT

0.10

AIT-81-4A

PPM H₂O

N/A

NT

0.10

AIT-80-2A

PPM THC

N/A

NT

0.10

LAB

PPM H₂

N/A

NT

0.20

Assay Results (by difference)

Nitrogen Min %

≥ 99.0 (Messer Spec ≥ 99.999%)

99.99985

NT = Not Tested

PPM O₂ Method Used: Electrochemical Manufacturer/Model#: Teledyne 3000TA-XL
PPM CO Method Used: Infrared Manufacturer/Model#: Siemens Ultramat 6

These analyzers have been validated by Messer as acceptable alternatives to the official NF for Nitrogen Assay. Validation study documentation is maintained by Messer at the corporate office. LIN NDA: 205766, LIN NADA: 14136

This document contains an electronic signature.

Analyst

Date

Sample Results Obtained from Messer Validated Analyzers

10/27/2025

Quality Reviewer

Date

John Doe

10/27/2025

Should the material not be delivered to an NF customer, the material is "Not Approved for Human Drug Use"

LOX1